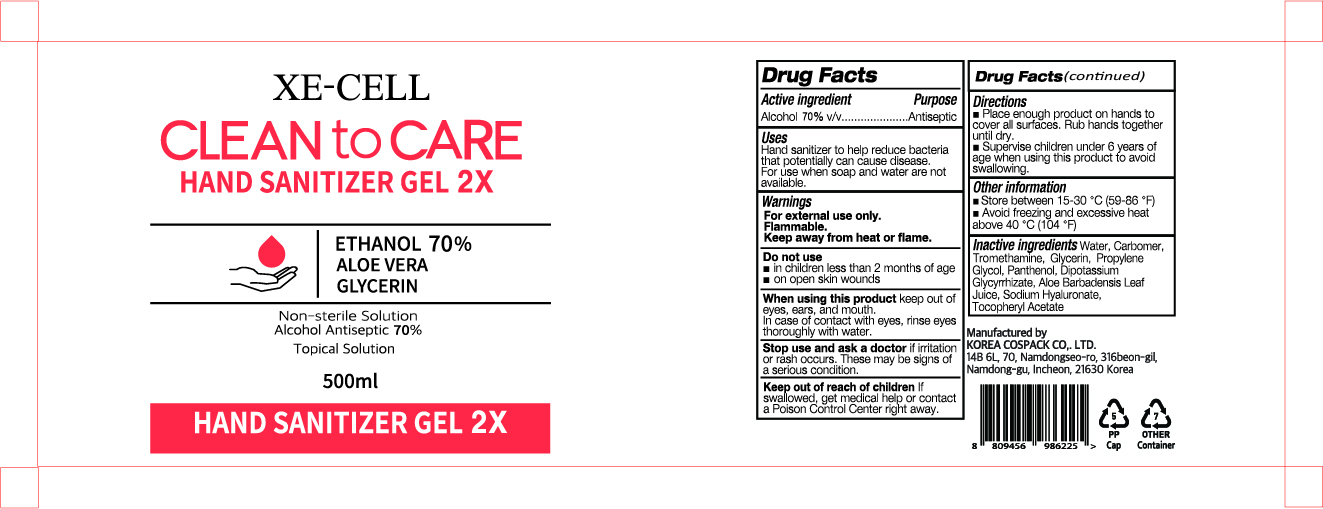 DRUG LABEL: CLEAN TO CARE HAND SANITIZER Gel
NDC: 74064-5070 | Form: GEL
Manufacturer: KOREA COSPACK CO.,LTD.
Category: otc | Type: HUMAN OTC DRUG LABEL
Date: 20200508

ACTIVE INGREDIENTS: ALCOHOL 350 mL/500 mL
INACTIVE INGREDIENTS: GLYCERIN; CARBOMER HOMOPOLYMER, UNSPECIFIED TYPE; WATER; PROPYLENE GLYCOL; PANTHENOL; GLYCYRRHIZINATE DIPOTASSIUM; ALOE VERA LEAF; .ALPHA.-TOCOPHEROL ACETATE; HYALURONATE SODIUM; TROLAMINE

CLEAN TO CARE HAND SANITIZER GEL 500 ml
74064-5070-1